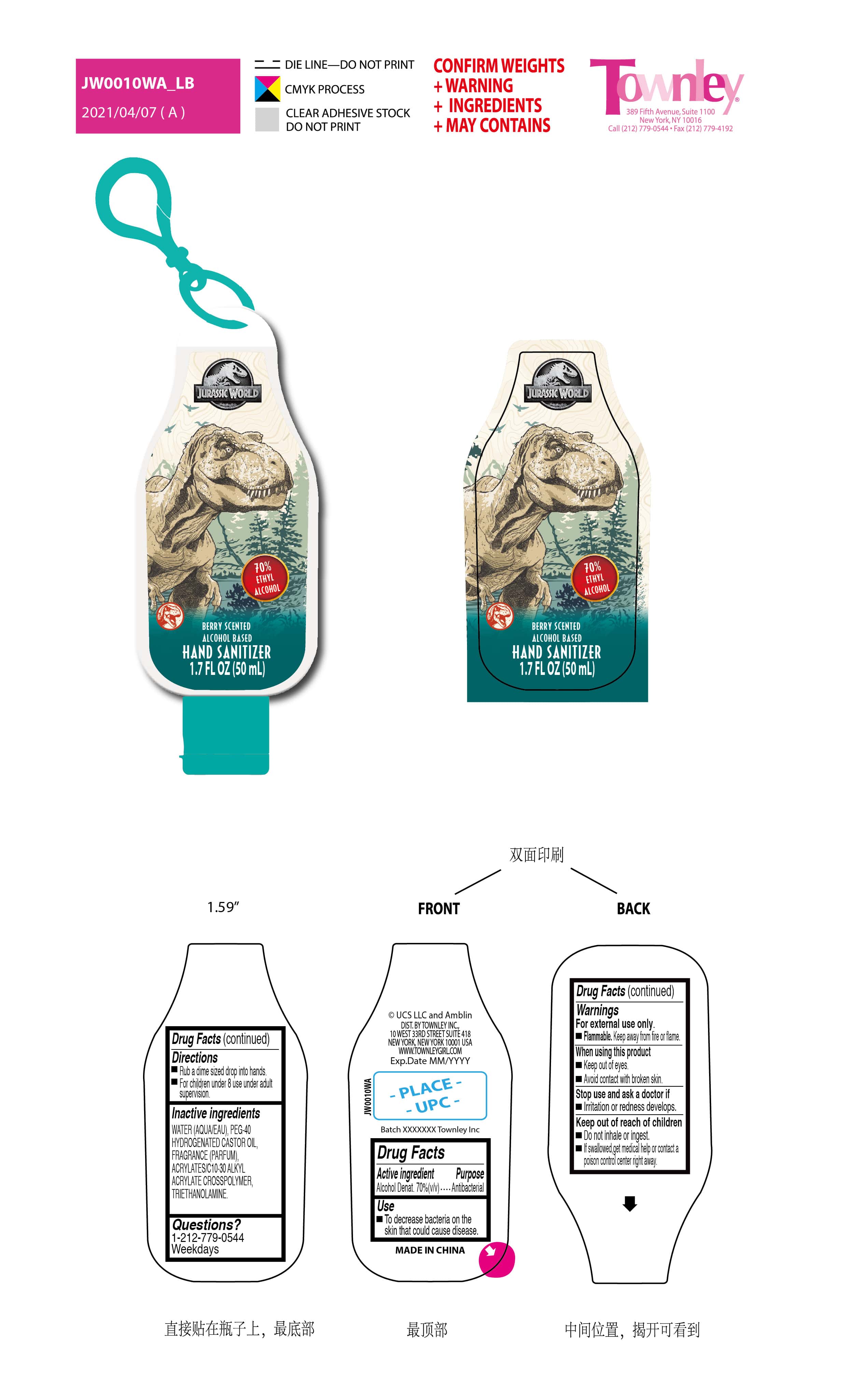 DRUG LABEL: berry scented hand sanitizer
NDC: 77901-047 | Form: GEL
Manufacturer: Foshan Astar Industry Co., Ltd
Category: otc | Type: HUMAN OTC DRUG LABEL
Date: 20210526

ACTIVE INGREDIENTS: ALCOHOL 70 mL/100 mL
INACTIVE INGREDIENTS: TROLAMINE 0.16 g/100 mL; WATER 36.2397 g/100 mL; GLYCOSMIS CITRIFOLIA WHOLE 0.2 g/100 mL; BILBERRY 0.2 mL/100 mL; POLYOXYL 40 HYDROGENATED CASTOR OIL 0.2 mL/100 mL

JW0010WA berry/ clear
Foshan Astar

Active ingredient Purpose

Alcohol Denat. 70%(v/v)..... Antibacterial

Use

To decrease bacteria on the skin that could cause disease.

Warnings

For external use only.

Flammable. Keep away from fire or flame.

When using this product

- Keep out of eyes.
- Avoid contact with broken skin.

Stop use and ask a doctor if

- Irritation or redness develops.

Keep out of reach of children

- Do not inhale or ingest
- if swallowed, get medical help or contact a poison control center right away.

Direction

Rub a dime sized drop into hands.

INDICATIONS AND USAGE

For children under 8 use under adult supervision

Inactive ingredients

WATER(AQUA/EAU), PEG-40 HYDROGENATED CASTOR OIL, FRAGRANCE(PARFUM), ACRYLATES/ C10-30 ALKYL ACRYLATE CROSSPOLYMER, TRIETHANOLAMINE.

Questions?

1-212-779-0544 weekdays